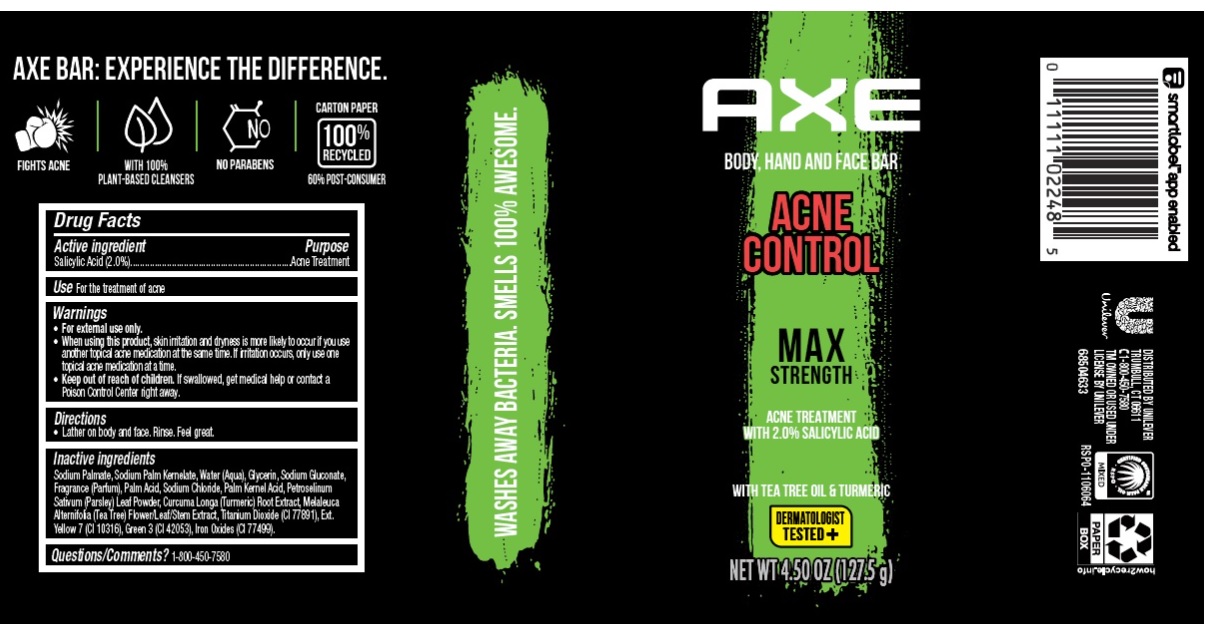 DRUG LABEL: Axe
NDC: 64942-2025 | Form: SOAP
Manufacturer: Conopco Inc. d/b/a/ Unilever
Category: otc | Type: HUMAN OTC DRUG LABEL
Date: 20241107

ACTIVE INGREDIENTS: SALICYLIC ACID 2 g/100 g
INACTIVE INGREDIENTS: EXT. D&C YELLOW NO. 7; SODIUM PALMATE; SODIUM PALM KERNELATE; GLYCERIN; SODIUM GLUCONATE; PALM ACID; TITANIUM DIOXIDE; PALM KERNEL ACID; PARSLEY; SODIUM CHLORIDE; WATER; FERRIC OXIDE RED; FD&C GREEN NO. 3

Axe Acne Control Body, Hand and Face Bar

AXE ACNE CONTROL BODY, HAND AND FACE BAR - Salicylic Acid

Dove Care & Protect Antibacterial Beauty Bar

Drug Facts

Active ingredient

Salicylic Acid (2.0)

Purpose

Acne Treatment

Uses

For the treatment of acne

Warnings

• For external use only
• When using this product, skin irritation and dryness is more likely to occur if you use anoter tropical acne medication at the same time. If irritation occurs, only use one tropical acne medication at a time.

• Keep out of reach of children except under adult supervision.

If swallowed, get medical help or contact a poison control Center right away.

Directions

Lather on body and face. Rinse. Feel great.

Inactive ingredients

Sodium Palmate, Sodium Palm Kernelate, Water (Aqua), Glycerin, Sodium Gluconate, Fragrance (Parfum), Palm Acid, Sodium Chloride, Palm Kernel Acid, Petroselinum Sativum (Parsley) Leaf Powder, Curcuma Longa (Tumeric) Root Extract, Melaleuca Alternifolia (Ta Tree) Flower/Leaf/Stem Extract, Titanium Dioxide (CI 77891), Ext. Yellow 7 (CI 42053), Iron Oxides (CI 77499).

Question/Comments?

1-800-450-7580